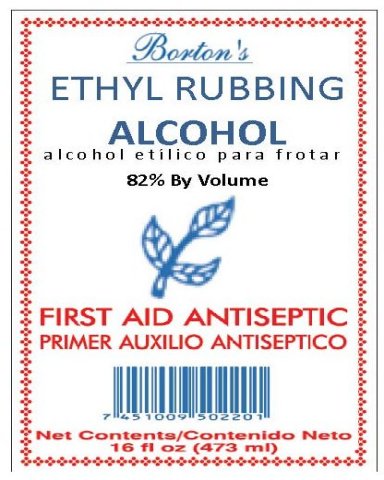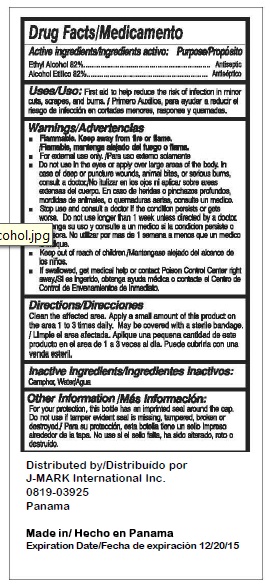 DRUG LABEL: Bortons Ethyl Rubbing Alcohol
NDC: 50790-100 | Form: LIQUID
Manufacturer: J-Mark International Inc. 
Category: otc | Type: HUMAN OTC DRUG LABEL
Date: 20100514

ACTIVE INGREDIENTS: ALCOHOL 82 mL/100 mL
INACTIVE INGREDIENTS: WATER

Borton's Ethyl Rubbing Alcohol

Drug Facts

Active Ingredients Purpose

Ethyl Alcohol 82 percent Antiseptic

Uses

First aid to help reduce the risk of infection in minor cuts, scrapes, and burns.

Warnings

Flammable. Keep away from fire or flame. For external use only. Do not use in the eyes or apply over large areas of the body. In case of deep or puncture wounds, animal bites, or serious burns, consult a doctor. Stop use and consult a doctor if the condition persists or gets worse. Do not use longer than 1 week unless directed by a doctor. Keep out of reach of children. If swallowed, get medical help or contact Poison Control Center right away.

Directions

Clean the affected area. Apply a small amount of this product on the area 1 ti 3 times daily. May be covered with a sterile bandage.

Inactive Ingredients

Camphor, Water

Other Information

For your protection, this bottle has an imprinted seal around the cap. Do not use if tamper evident seal is missing, tampered, broken, or destroyed.

DESCRIPTION

Distributed by/Distribuido por

J-MARK International Inc.

0819-03925

Panama

Made In/Hecho en Panama

Expiration Date/Fecha de Expiracion 12/20/15

PACKAGE LABEL

Borton's ETHYL RUBBING ALCOHOL 82 percent By Volume FIRST AID ANTISEPTIC Net Contents 16 fl oz (473 ml)